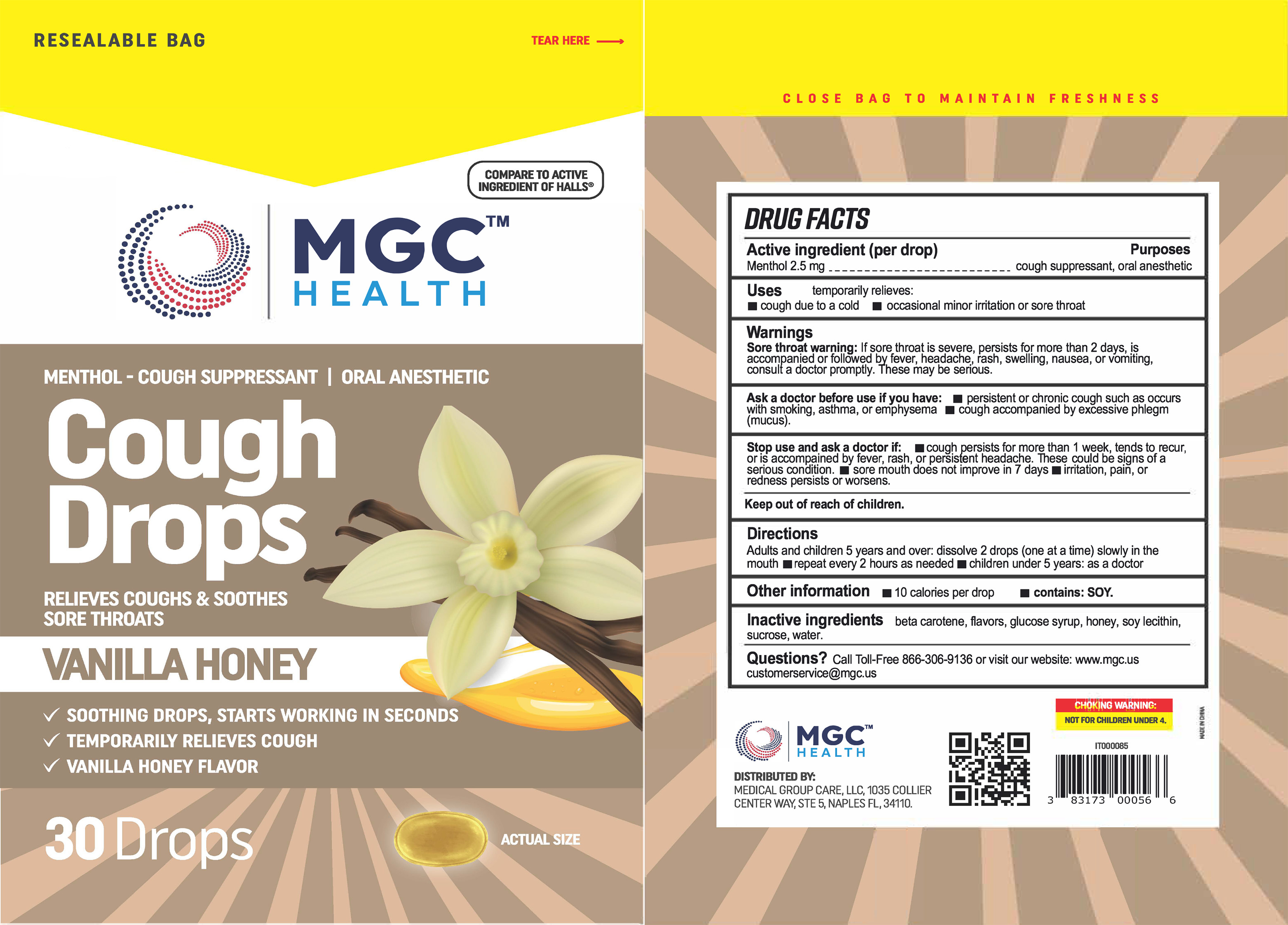 DRUG LABEL: MGC Health
NDC: 83698-128 | Form: LOZENGE
Manufacturer: Xiamen Kang Zhongyuan Biotechnology Co., Ltd.
Category: otc | Type: HUMAN OTC DRUG LABEL
Date: 20251229

ACTIVE INGREDIENTS: MENTHOL 2.5 mg/1 1
INACTIVE INGREDIENTS: CORN SYRUP; WATER; LECITHIN, SOYBEAN; HONEY; SUCROSE; BETA CAROTENE

YNBY-MGC VH Drops 30 2023

Active Ingredient(s)

Menthol 2.5

Purpose

Purposes cough suppressant, oral anesthetic

Use

temporary relieves: ■ cough due to cold ■ occasional minor irritation or sore throat

Warnings

Sore throat warning: If sore throat is severe, persists for more than 2 days, is accompanied or follow headache, rash, swelling, nausea, or vomiting, consult a doctor promptly. These may be serious.

Ask a doctor before use if you have: ■ persistent or chronic cough such as occurs with smoking, asthma, or emphysema ■ cough accompanied by excessive phlegm (mucus).

Stop use and ask a doctor if ■ cough persists for more than 1 week, tends to recur, or is accompained by fever, rash, or persistent headache. These could be signs of a serius condition. ■ sore mouth does not improve in 7 days ■ irritation, pain, or redness persists or worsens.

Keep out of reach of children.

Directions

Adults and children 5 years and over: dissolve 2 drops (one at a time) slowly in the mouth repeat every 2 hours as needed

children under 5 years: as a doctor

Other information

■ 10 calories per drop ■ contains: SOY.

Inactive ingredients

beta carotene, flavors, glucose syrup, honey, soy lecithin, sucrose, water.

QUESTIONS

Call Toll-Free 866-306-9136 or visit our website: www.mac.us

customerservice@mgc.Us

Package Label - Principal Display Panel

30 Drops NDC: 61658-128-30